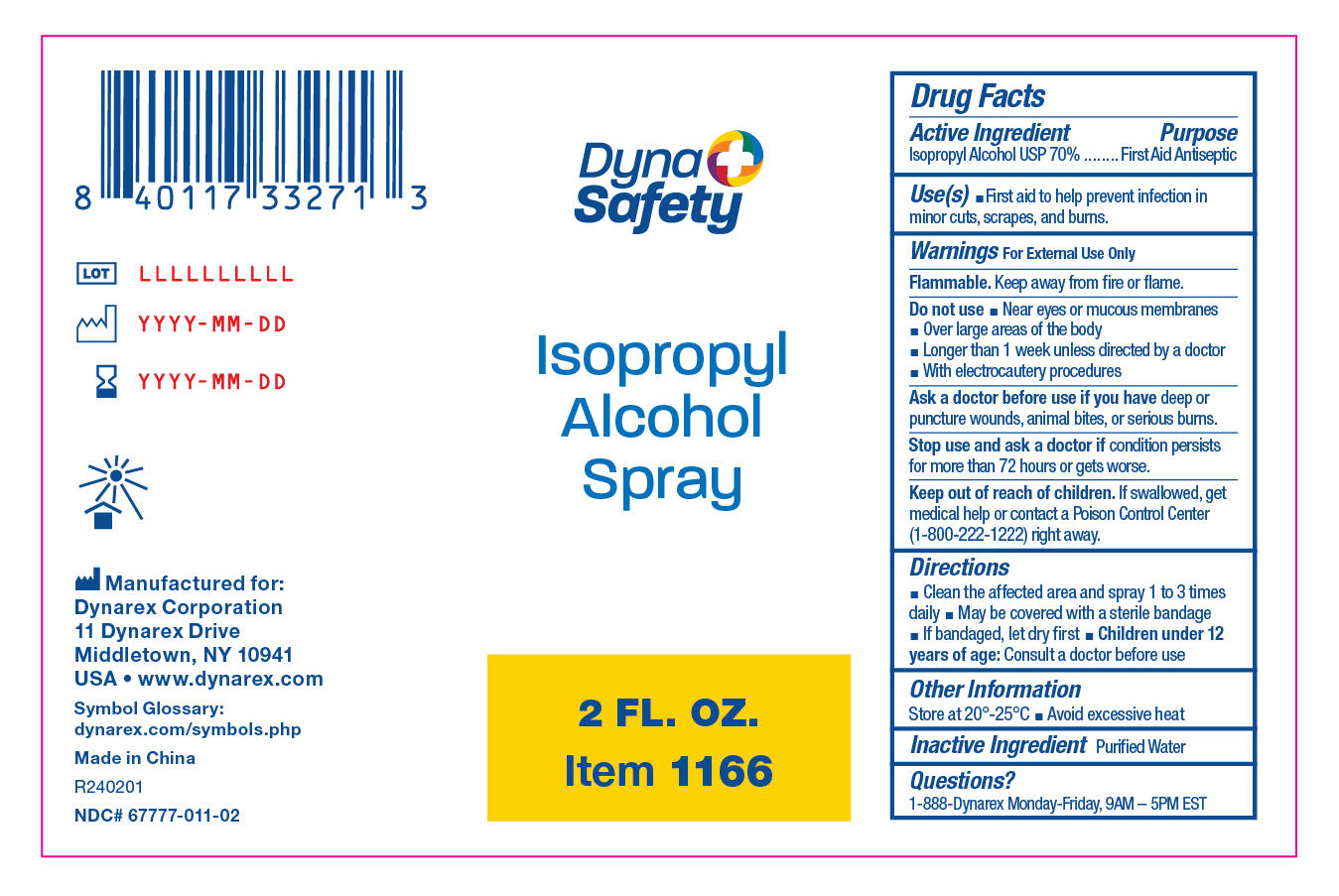 DRUG LABEL: Isopropyl Alcohol
NDC: 67777-011 | Form: SPRAY
Manufacturer: Dynarex Corporation
Category: otc | Type: HUMAN OTC DRUG LABEL
Date: 20240215

ACTIVE INGREDIENTS: ISOPROPYL ALCOHOL 0.7 mL/1 mL
INACTIVE INGREDIENTS: WATER

1166 Isopropyl Alcohol Spray

Active Ingredient

Isopropyl Alcohol 70%

Purpose

First Aid Antiseptic

Use(s)

• First aid to help prevent infection in minor cuts, scrapes, and burns.

Warnings

For External Use Only

Do not use

• Near eyes or mucous membranes • Over large areas of the body • Longer than 1 week unless directed by a doctor • With electrocautery procedures

Ask a doctor before use if you have

Deep or puncture wounds, animal bites, or serious burns.

Stop use and ask a doctor if

Condition persists for more than 72 hours or get worse.

Keep out of reach of children

If swallowed, get medical help or contact a Poison Control Center (1-800-222-1222) right away.

Directions

• Clean the affected area and spray 1 to 3 times daily • May be covered with a sterile bandage • If bandaged, let dry first

• Children under 12 years of age: Consult a doctor before use

Other Information

• Store at 20º-25ºC

• Avoid excessive heat

Inactive Ingredient

Purified Water

Questions?

1-888-Dynarex Monday - Friday, 9AM - 5PM EST

Label 1166

Isopropyl Alcohol Spray